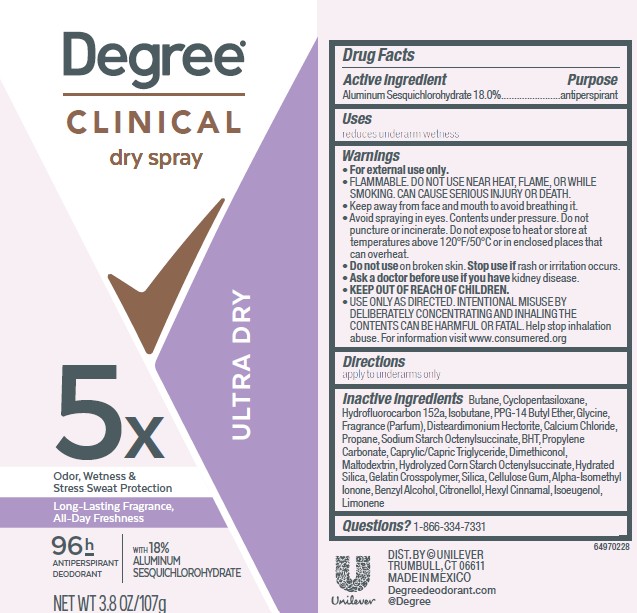 DRUG LABEL: Degree
NDC: 64942-2392 | Form: AEROSOL, SPRAY
Manufacturer: Conopco, Inc. d/b/a Unilever
Category: otc | Type: HUMAN OTC DRUG LABEL
Date: 20251202

ACTIVE INGREDIENTS: ALUMINUM SESQUICHLOROHYDRATE 18 g/100 g
INACTIVE INGREDIENTS: BHT; CAPRYLIC/CAPRIC TRIGLYCERIDE; BENZYL ALCOHOL; CITRONELLOL; LIMONENE, (+)-; SILICA; PPG-14 BUTYL ETHER; GLYCINE; PROPANE; ALPHA-ISOMETHYL IONONE; CYCLOPENTASILOXANE; HYDROFLUOROCARBON 152A; HYDRATED SILICA; ISOBUTANE; CALCIUM CHLORIDE; CELLULOSE GUM; ISOEUGENOL; HEXYL CINNAMAL; PROPYLENE CARBONATE; BUTANE; DISTEARDIMONIUM HECTORITE; MALTODEXTRIN; DIMETHICONOL (40 CST)

Degree Clinical Dry Spray Ultra Dry 96H Antiperspirant Deodorant

DESCRIPTION

Degree Clinical Dry Spray Ultra Dry 96H Antiperspirant Deodorant

ACTIVE INGREDIENT

Aluminum Sesquichlorohydrate 18.0%

PURPOSE

antiperspirant

INDICATIONS AND USAGE

reduces underarm wetness

WARNINGS

For external use only.
FLAMMABLE. DO NOT USE NEAR HEAT, FLAME, OR WHILE SMOKING. CAN CAUSE SERIOUS INJURY OR DEATH.
Keep away from face and mouth to avoid breathing in.
Avoid spraying in eyes. Contents under pressure. Do not puncture or incinerate. Do not expose to heat or store at temperatures above 120°F/50°C or in enclosed places that could overheat.
Do not use on broken skin. Stop use if rash or irritation occurs.
Ask a doctor before using if you have kidney disease.
USE ONLY AS DIRECTED. INTENTIONAL MISUSE BY DELIBERATELY CONCENTRATING AND INHALING THE CONTENTS CAN BE HARMFUL OR FATAL. Help stop inhalation abuse. For information visit www.consumered.org

KEEP OUT OF REACH OF CHILDREN.

DOSAGE AND ADMINISTRATION

apply to underarms only

INACTIVE INGREDIENT

Butane,Cyclopentasiloxane, Hydrofluorocarbon 152a,Isobutane,PPG-14 Butyl Ether,Glycine, Fragrance (Parfum),Disteardimonium Hectorite,Calcium Chloride, Propane,Sodium Starch Octenylsuccinate,BHT,Propylene Carbonate,Caprylic/Capric Triglyceride,Dimethiconol, Maltodextrin,Hydrolyzed Corn Starch Octenylsuccinate,Hydrated Silica,Gelatin Crosspolymer,Silica,Cellulose Gum,Alpha-Isomethyl Ionone,Benzyl Alcohol,Citronellol,Hexyl Cinnamal,Isoeugenol, Limonene

QUESTIONS

1-866-334-7331